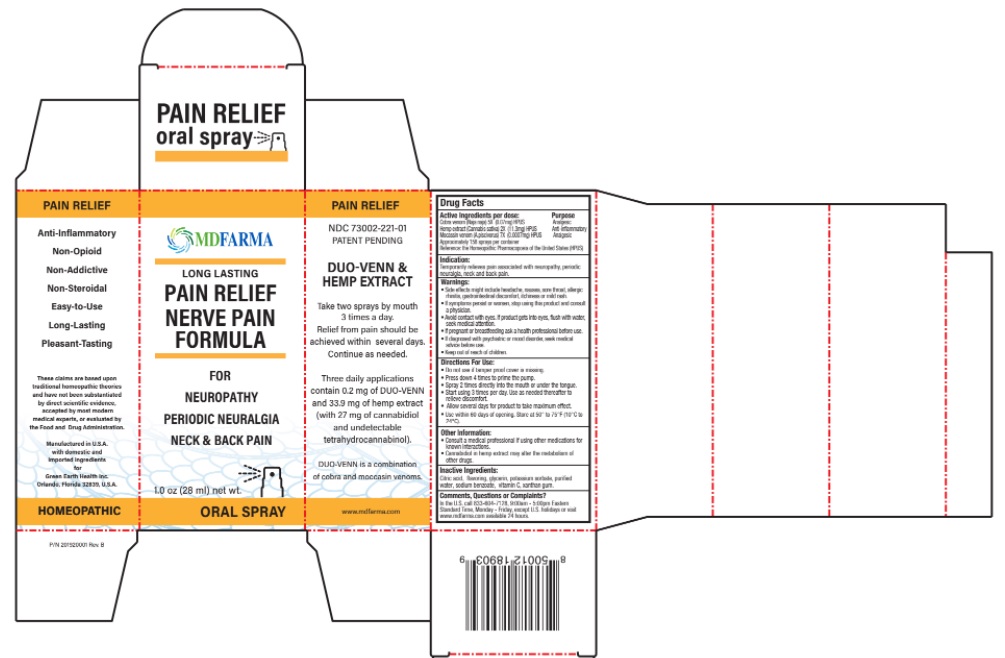 DRUG LABEL: PAIN RELIEF SNAKE VENOM AND HEMP
NDC: 73002-221 | Form: SPRAY
Manufacturer: Green Earth Health Inc.
Category: homeopathic | Type: HUMAN OTC DRUG LABEL
Date: 20250723

ACTIVE INGREDIENTS: NAJA NAJA VENOM 4 [hp_X]/1 mL; CANNABIS SATIVA SUBSP. SATIVA FLOWERING TOP 2 [hp_X]/1 mL; AGKISTRODON PISCIVORUS VENOM 6 [hp_X]/1 mL
INACTIVE INGREDIENTS: ANHYDROUS CITRIC ACID; SIRAITIA GROSVENORII FRUIT; TEA LEAF; GLYCERIN; POTASSIUM SORBATE; WATER; SODIUM BENZOATE; ASCORBIC ACID; XANTHAN GUM

Drug Facts

Active Ingredients Purpose

Cobra venom (Naja naja) 5X (0.07mg) HPUS Analgesic
Hemp extract (Cannabis sativa) 2X (11.3mg) HPUS Anti-inflammatory
Moccasin venom (A.piscivorus) 7X (0.0007mg) HPUS Analgesic

Approximately 158 sprays per container

Reference: the Homeopathic Pharmacopoeia of the United States (HPUS)

Indication:

Temporarily relieves pain associated with neuropathy, periodic neuralgia, neck & back pain

Warnings:

• Side effects might include headache, nausea, sore throat, allergic rhinitis, gastrointestinal discomfort, itchiness or mild rash.
• If symptoms persist or worsen, stop using this product and consult a physician.
• Avoid contact with eyes. If product gets into eyes, flush with water, seek medical attention.
• If pregnant or breastfeeding ask a health professional before use.
• If diagnosed with psychiatric or mood disorder, seek medical advice before use.
• Keep out of reach of children.

Directions For Use:

- Do not use if tamper proof cover is missing.
- Press down 4 times to prime the pump.
- Spray 2 times directly into the mouth or under the tongue.
- Start using 3 times per day. Use as needed thereafter to relieve discomfort.
- Allow several days for product to take maximum effect.
- Use within 60 days from opening. Store at 50° to 75°F (10°C to 24°C)

Other Information:

- Consult medical professional if using other medications for known interactions.
- Cannabidiol in hemp extract may alter the metabolism of other drugs.

Inactive Ingredients:

Citric acid, flavoring, glycerin, potassium sorbate, purified water, sodium benzoate, vitamin C, xanthan gum.